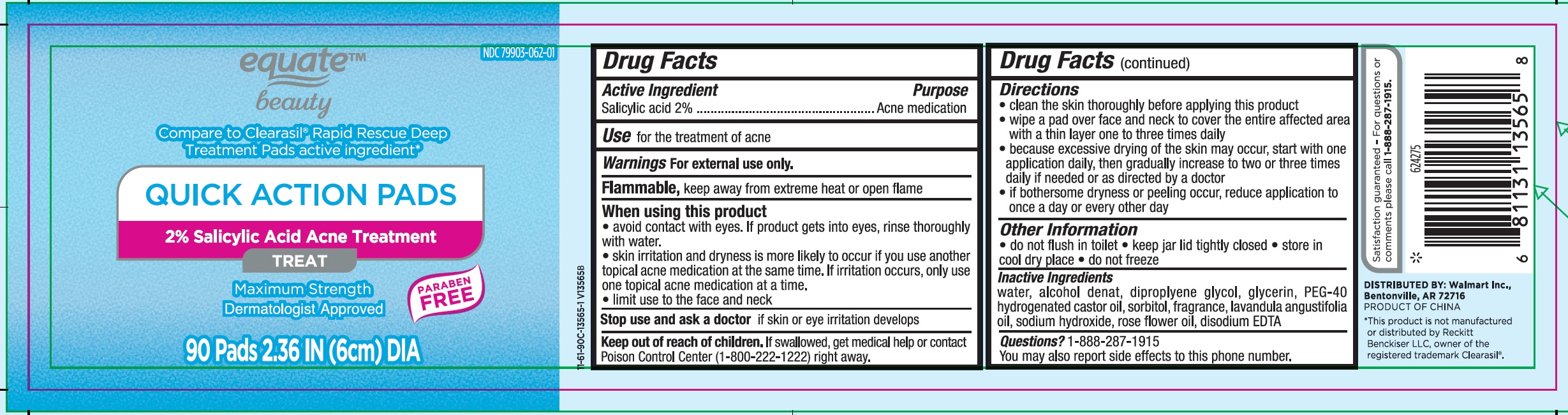 DRUG LABEL: Equate Beauty Quick Action Pads Salicylic Acid Acne Treatment
NDC: 61805-117 | Form: CLOTH
Manufacturer: Bath Concept Cosmetics (Dongguan) Co., Ltd
Category: otc | Type: HUMAN OTC DRUG LABEL
Date: 20231026

ACTIVE INGREDIENTS: SALICYLIC ACID 20 mg/1 mL
INACTIVE INGREDIENTS: WATER; ALCOHOL; DIPROPYLENE GLYCOL; GLYCERIN; POLYOXYL 40 HYDROGENATED CASTOR OIL; SORBITOL; LAVENDER OIL; SODIUM HYDROXIDE; EDETATE DISODIUM ANHYDROUS; ROSE OIL

Equate Beauty Quick Action Pads 2% Salicylic Acid Acne Treatment

Active Ingredient

Salicylic acid 2%

Purpose

Acne medication

Use

for the treatment of acne

Warnings

For external use only.

keep away from extreme heat or open flame Flammable,

When using this product

- avoid contact with eyes. If product gets into eyes, rinse thoroughly with water.
- skin irritation and dryness is more likely to occur if you use another topical acne medication at the same time. If irritation occurs, only use one topical acne medication at a time.
- limit use to the face and neck

Stop use and ask a doctor

if skin or eye irritation develops

Keep out of reach of children.

If swallowed, get medical help or contact Poison Control Center (1-800-222-1222) right away.

Directions

- clean the skin thoroughly before applying this product
- wipe a pad over face and neck to cover the entire affected area with a thin layer one to three times daily
- because excessive drying of the skin may occur, start with one application daily, then gradually increase to two or three times daily if needed or as directed by a doctor
- if bothersome dryness or peeling occur, reduce application to once a day or every other day

Other Information

- do not flush to toilet
- keep jar lid tightly closed
- store in cool dry place
- do not freeze

Inactive Ingredients

water, alcohol denat, dipropylene glycol, glycerin, PEG-40 Hydrogenated castor oil, sorbitol, fragrance, lavandula angustifolia oil, sodium hydroxide, rose flower oil, disodium EDTA

Questions?

1-888-287-1915

You may also report side effects to this phone number.